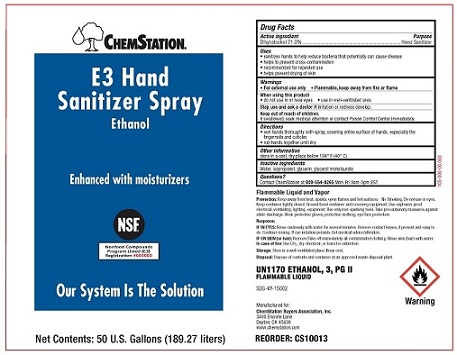 DRUG LABEL: ChemStation E3 Hand Sanitizer
NDC: 71212-100 | Form: LIQUID
Manufacturer: Chemstation
Category: otc | Type: HUMAN OTC DRUG LABEL
Date: 20250109

ACTIVE INGREDIENTS: ALCOHOL 710 g/1 L
INACTIVE INGREDIENTS: GLYCERIN; GLYCERYL LAURATE; WATER; ISOPROPYL ALCOHOL

Chemstation E3 Hand Sanitizer Spray

Drug Facts

Active Ingredient

Ethyl alcohol 71.0%

Purpose

Hand Sanitizer

Uses

- sanitizes hands to help reduce bacteria that potentially can cause disease
- helps to prevent cross-contamination
- recommended for repeated use
- helps prevent drying of skin

Warnings

- For external use only
- Flammable, keep away from fire or flame

When using this product

- do not use in or near eyes
- use in well-ventilated area

Stop use and ask a doctor ifirritation or redness develop.

Keep out of reach of children.

If swallowed, seek medical attention or contact Poison Control Center immediately.

Directions

- wet hands thoroughly with spray, covering entire surface of hands, especially the fingernails and cuticles
- rub hands together until dry

Other information

store in a cool, dry place below 104° F (40° C)

Inactive Ingredients

Water, isopropanol, glycerin, glycerol monolaurate

Questions?

Contact Chemstation at 800-554-8265Mon-Fri 9am-5pm EST

OTHER SAFETY INFORMATION

Flammable Liquid and Vapor

Prevention:Keep away from heat, sparks, open flames and hot surfaces - No smoking. Do not use in the eyes. Keep container tightly closed. Ground/bond container and receiving equipment. Use explosion-proof electrical, ventilating, lighting, equipment. Use only non-sparking tools. Take precautionary measures against static discharge. Wear protective gloves, protective clothing, eye/face protection.

Response:

IF IN EYES:Rinse cautiously with water for several minutes. Remove contact lenses, if present and easy to do. Continue rinsing. If eye irritation persists: Get medical advice/attention.

IF ON SKIN (or hair):Remove/Take off immediately all contaminated clothing. Rinse skin (hair) with water.

In case of fire:Use CO2dry chemical, or foam for extinction.

Storage:Store in a well-ventilated place. Keep cool.

Disposal:Dispose of contents and container at an approved waste disposal plant.

Manufactured for:

ChemStation Buyers Association, Inc.

3400 Encrete Lane

Dayton, OH 45439

www.chemstation.com

PACKAGE LABEL

CHEMSTATION®

E3 Hand Sanitizer Spray

Ethanol

Enhanced with moisturizers

Our System Is The Solution

Net Contents: 50 U.S. Gallons (189.27 liters)